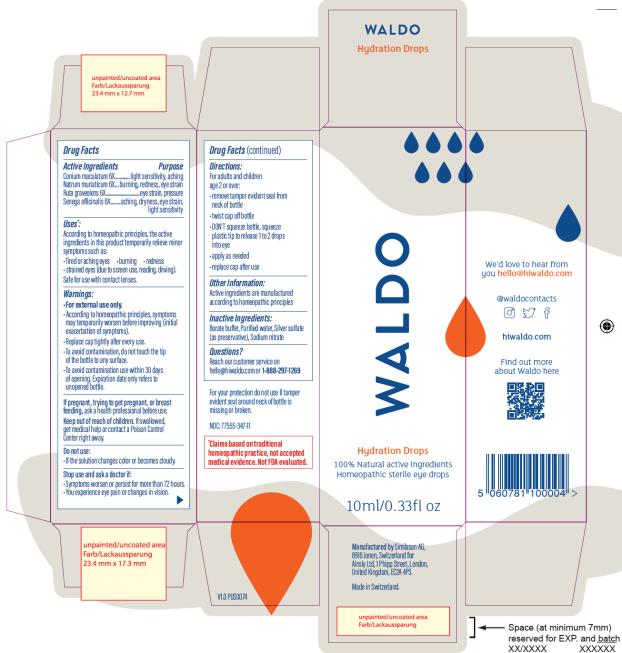 DRUG LABEL: Waldo Hydration Drops
NDC: 77555-347 | Form: LIQUID
Manufacturer: Ainsly Limited
Category: homeopathic | Type: HUMAN OTC DRUG LABEL
Date: 20220120

ACTIVE INGREDIENTS: CONIUM MACULATUM FLOWERING TOP 6 [hp_X]/1 mL; SODIUM CHLORIDE 6 [hp_X]/1 mL; RUTA GRAVEOLENS FLOWERING TOP 6 [hp_X]/1 mL; POLYGALA SENEGA ROOT 6 [hp_X]/1 mL
INACTIVE INGREDIENTS: WATER; SILVER SULFATE; SODIUM NITRATE

Waldo Hydration Drops

Drug Facts

Active Ingredients

Conium maculatum 6X

Purpose

light sensitivity, aching

Active Ingredients

Natrum muriaticum 6X

Purpose

burning, redness, eye strain

Active Ingredients

Ruta graveolens 6X

Purpose

eye strain, pressure

Active Ingredients

Senega officinalis 6X

Purpose

aching, dryness, eye strain, light sensitivity

Uses*

According to homeopathic principles, the active ingredients in this product temporarily relieve minor symptoms such as:

• tired or aching eyes

• burning

• redness

• strained eyes (due to screen use, reading, driving)

Safe for use with contact lenses.

Warnings

• For external use only.

• According to homeopathic principles, symptoms may temporarily worsen before improving (Initial exacerbation of symptoms).

• Replace cap tightly after every use.

• To avoid contamination, do not touch the tip of the bottle to any surface.

• To avoid contamination use within 30 days of opening. Expiration date only refers to unopened bottle.

If pregnant, trying to get pregnant or breast feeding,

ask a health professional before use.

Keep out of reach of children.

If swallowed, get medical help or contact a Poison Control Center right away.

Do not use:

• if the solution changes color or becomes cloudy.

Stop use and ask a doctor if:

• symptoms worsen or persist for more than 72 hours

• you experience eye pain or changes in vision

Directions

For adults and children age 2 and over:

• remove tamper-evident seal from neck of bottle

• twist cap off bottle

• DON'T squeeze bottle, squeeze plastic tip to release 2 to 3 drops into eye

• apply as needed

• replace cap after use

Other Information

Active ingredients are manufactured according to homeopathic principles.

Inactive Ingredients

Borate buffer, Purified water, Silver sulfate (as preservative), Sodium nitrate

Questions?

Reach our customer service on hello@hiwaldo.com or 1-888-297-1269

For your protection do not use if tamper evident seal around neck of bottle is missing or broken.

NDC: 77555-347-11

*Claims based on traditional homeopathic practice, not accepted medical evidence. Not FDA evaluated.

PRINCIPAL DISPLAY PANEL

Waldo
Hydration Drops
100% Natural active ingredients

Homeopathic sterile eye drops
10 ml/ 0.33 fl oz